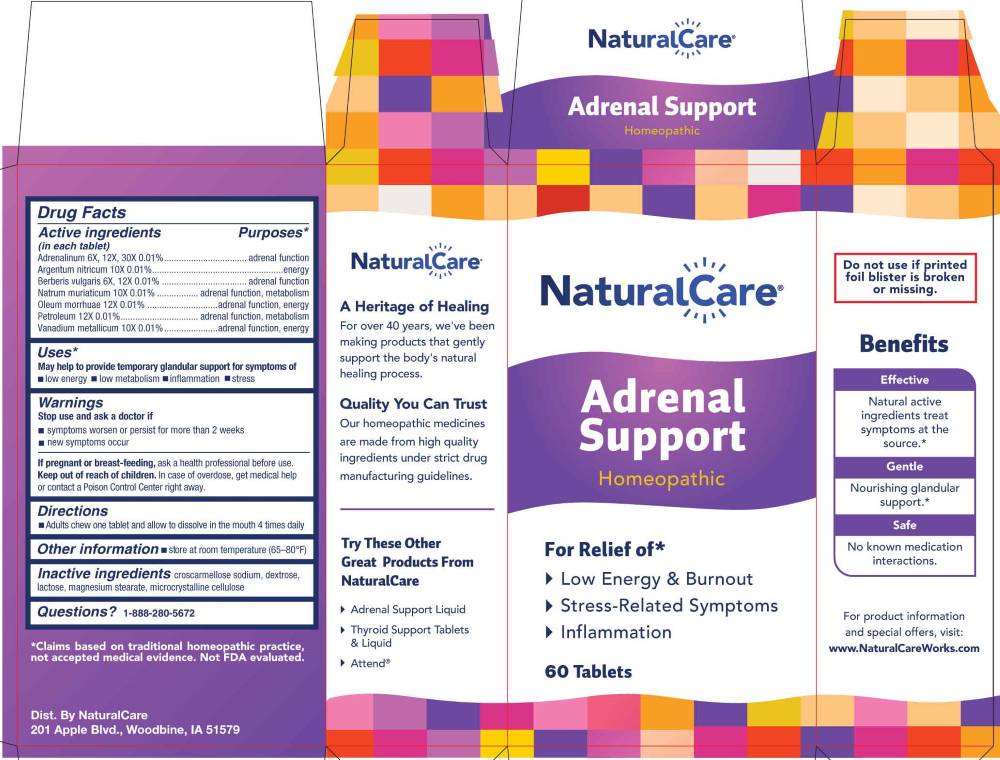 DRUG LABEL: Adrenal Support
NDC: 70163-0026 | Form: TABLET
Manufacturer: NaturalCare
Category: homeopathic | Type: HUMAN OTC DRUG LABEL
Date: 20260130

ACTIVE INGREDIENTS: EPINEPHRINE 6 [hp_X]/1 1; BERBERIS VULGARIS ROOT BARK 6 [hp_X]/1 1; SILVER NITRATE 10 [hp_X]/1 1; SODIUM CHLORIDE 10 [hp_X]/1 1; VANADIUM 10 [hp_X]/1 1; COD LIVER OIL 12 [hp_X]/1 1; KEROSENE 12 [hp_X]/1 1
INACTIVE INGREDIENTS: CROSCARMELLOSE SODIUM; DEXTROSE, UNSPECIFIED FORM; LACTOSE MONOHYDRATE; MAGNESIUM STEARATE; MICROCRYSTALLINE CELLULOSE

DRUG FACTS:

ACTIVE INGREDIENT:

(in each tablet) Adrenalinum 6X, 12X, 30X 0.01%, Argentum Nitricum 10X 0.01%, Berberis Vulgaris 6X, 12X 0.01%, Natrum Muriaticum 10X 0.01%, Oleum Morrhuae 12X 0.01%, Petroleum 12X 0.01%, Vanadium Metallicum 10X 0.01%.

PURPOSE:

Adrenalinum – adrenal function, Argentum Nitricum - energy, Berberis Vulgaris – adrenal function, Natrum Muriaticum – adrenal function, metabolism, Oleum Morrhuae – adrenal function, energy, Petroleum – adrenal function, metabolism, Vanadium Metallicum – adrenal function, energy*

*Claims based on traditional homeopathic practice, not accepted medical evidence. Not FDA evaluated.

USES:

May help to provide temporary glandular support for symptoms of

• low energy • low metabolism • inflammation • stress*

*Claims based on traditional homeopathic practice, not accepted medical evidence. Not FDA evaluated.

WARNINGS:

Stop use and ask a doctor if

•symptoms worsen or persist for more than 2 weeks

• new symptoms occur

If pregnant or breast-feeding, ask a health professional before use.

Keep out of reach of children. In case of overdose, get medical help or contact a Poison Control Center right away.

Do not use if printed foil blister is broken or missing.

• Store at room temperature (65-80ºF)

KEEP OUT OF REACH OF CHILDREN:

In case of overdose, get medical help or contact a Poison Control Center right away.

DIRECTIONS:

• Adults chew one tablet and allow to dissolve in the mouth 4 times daily

INACTIVE INGREDIENTS:

croscarmellose sodium, dextrose, lactose, magnesium stearate, microcrystalline cellulose

QUESTIONS:

Dist. By NaturalCare

201 Apple Blvd.

Woodbine, IA 51579

www.NaturalCareWorks.com

1-888-280-5672

PACKAGE LABEL DISPLAY:

NaturalCare

Adrenal Support

Homeopathic

For Relief of*

Low Energy & Burnout

Stress-Related symptoms

Inflammation

60 Tablets